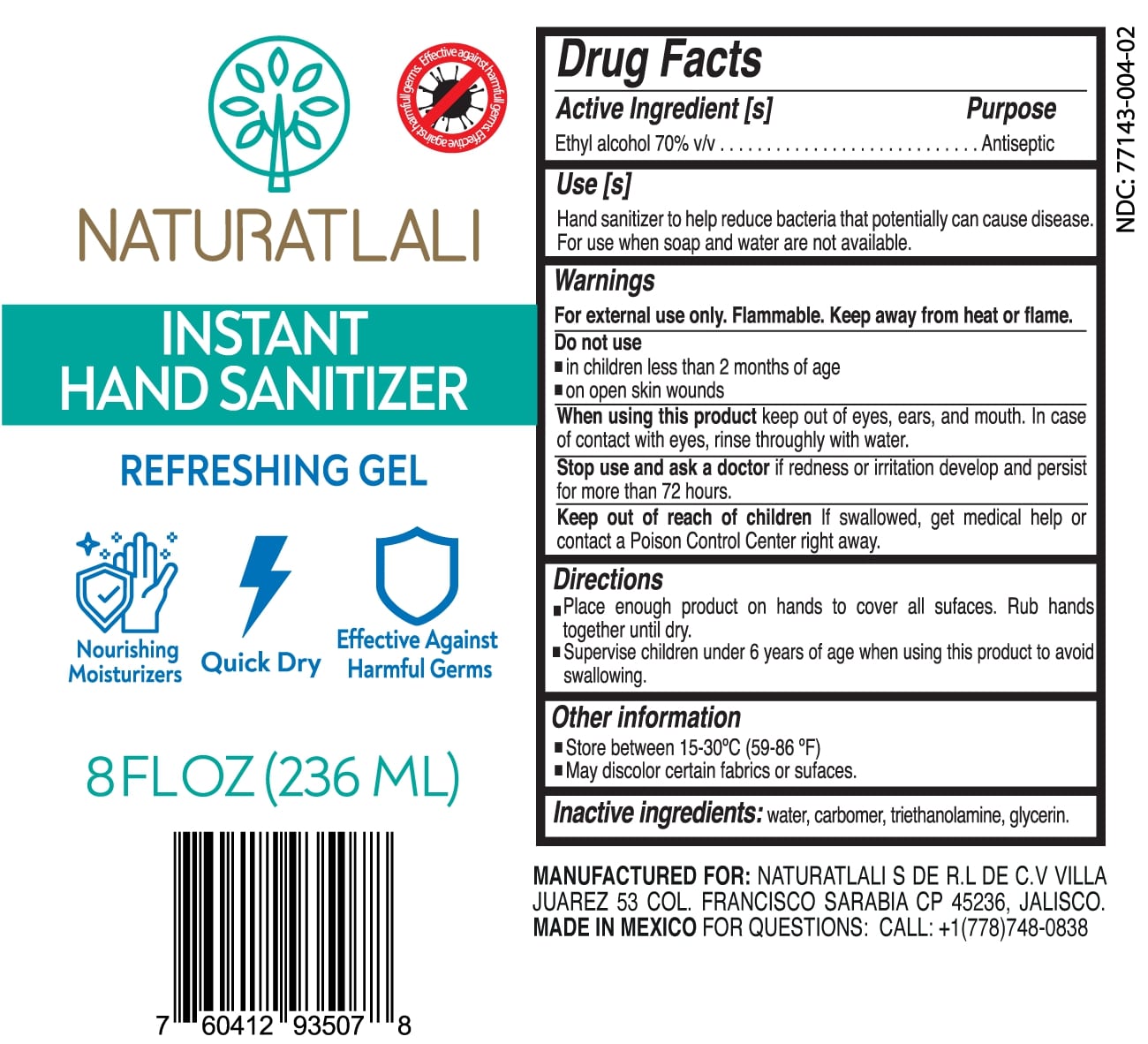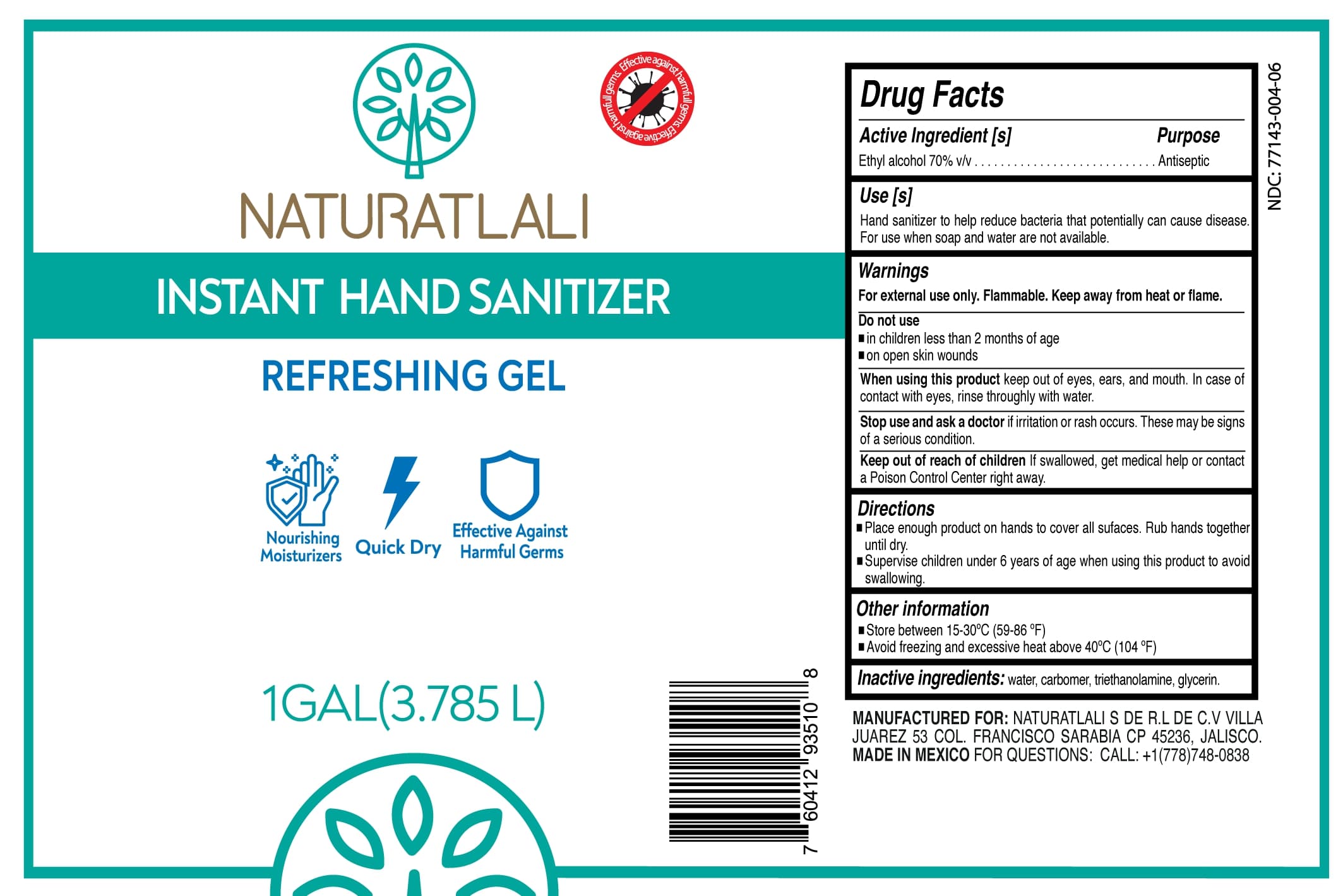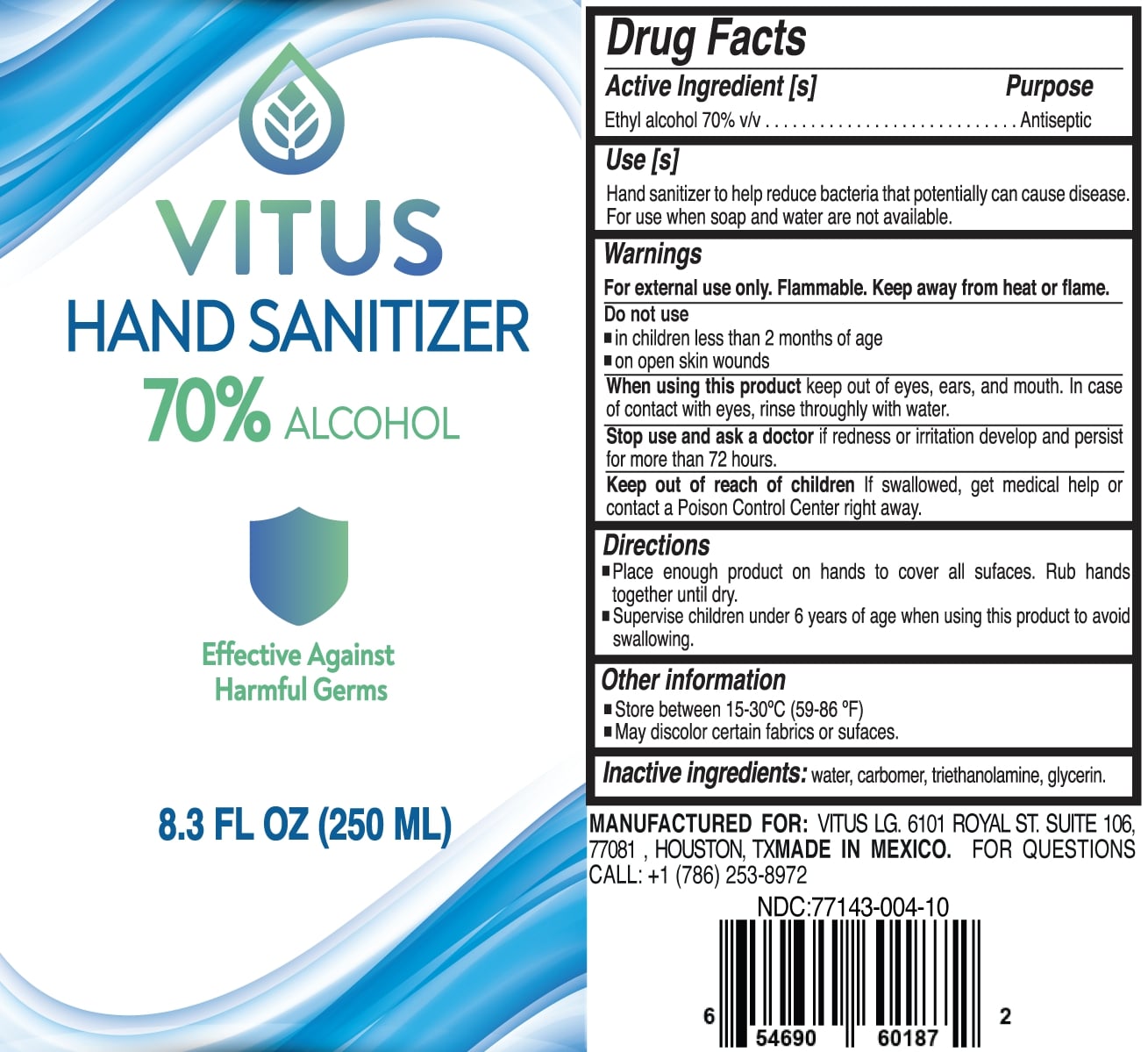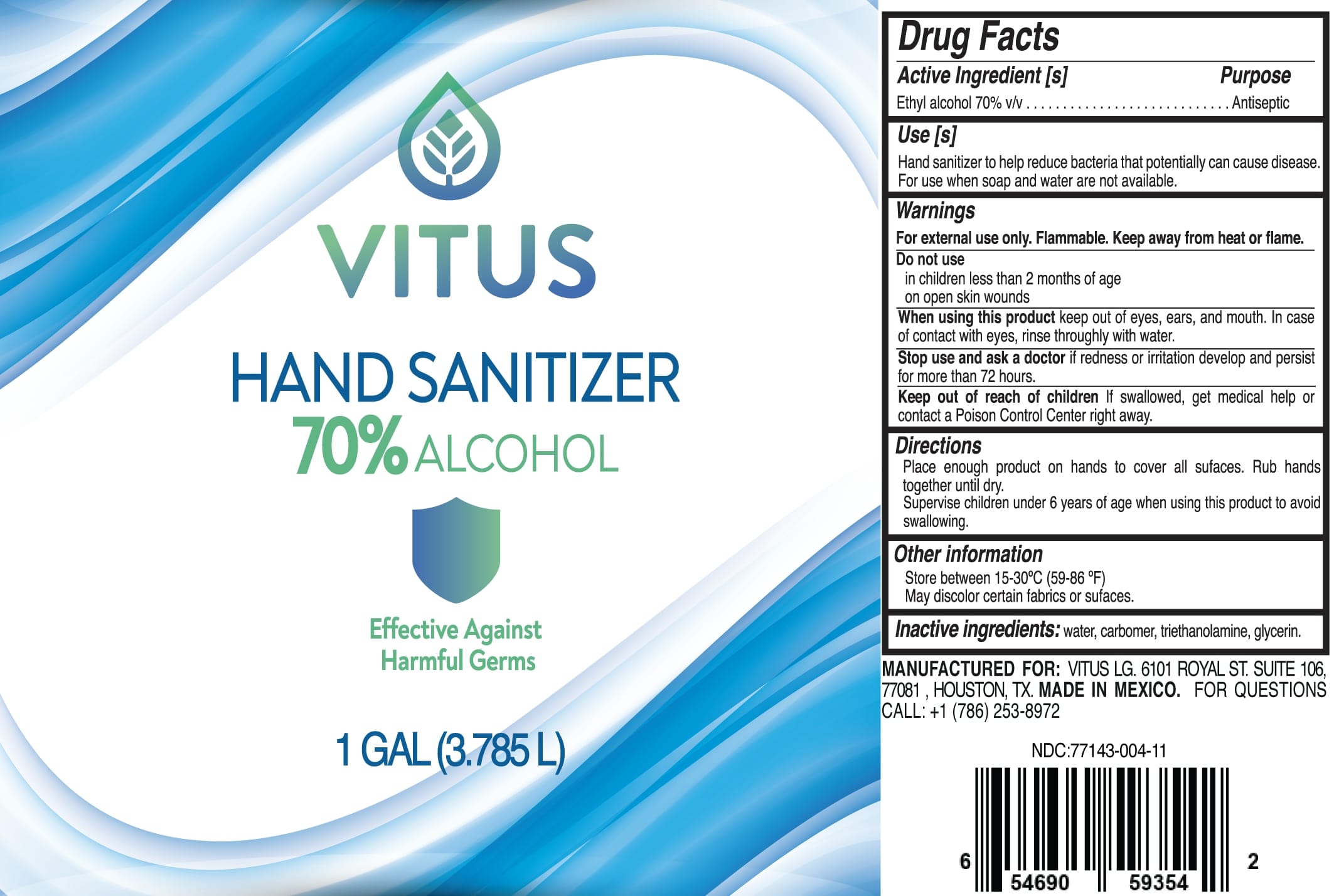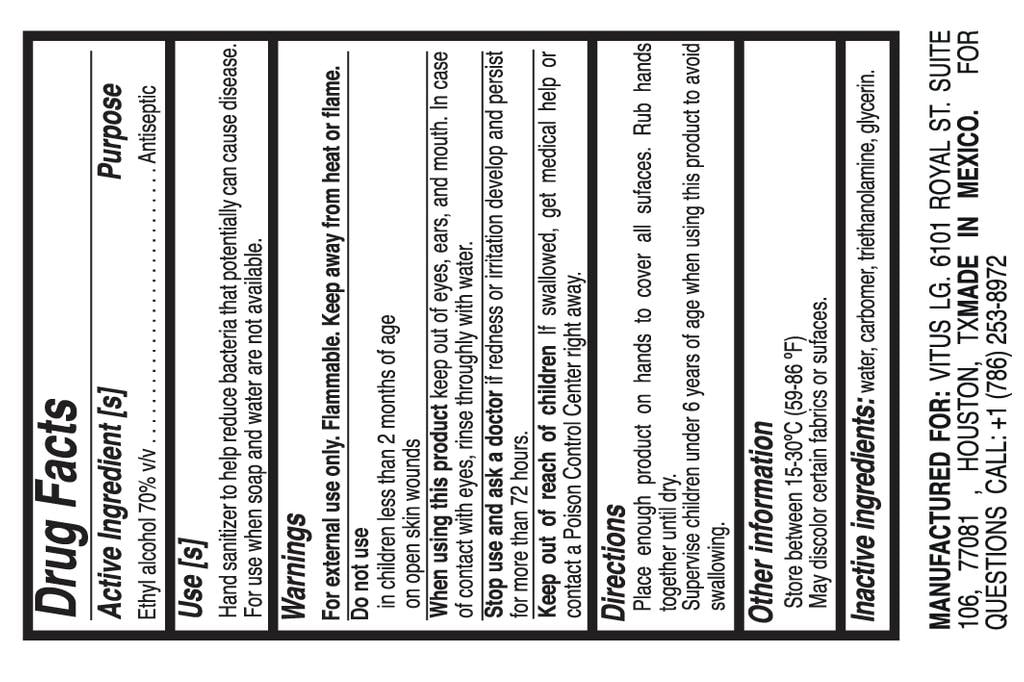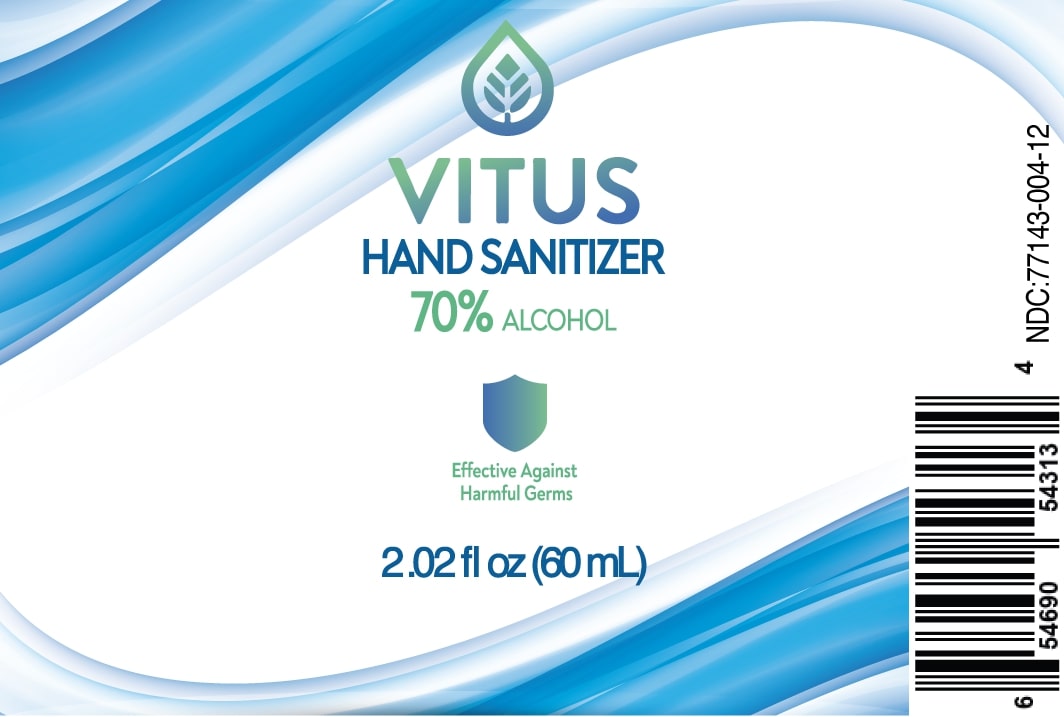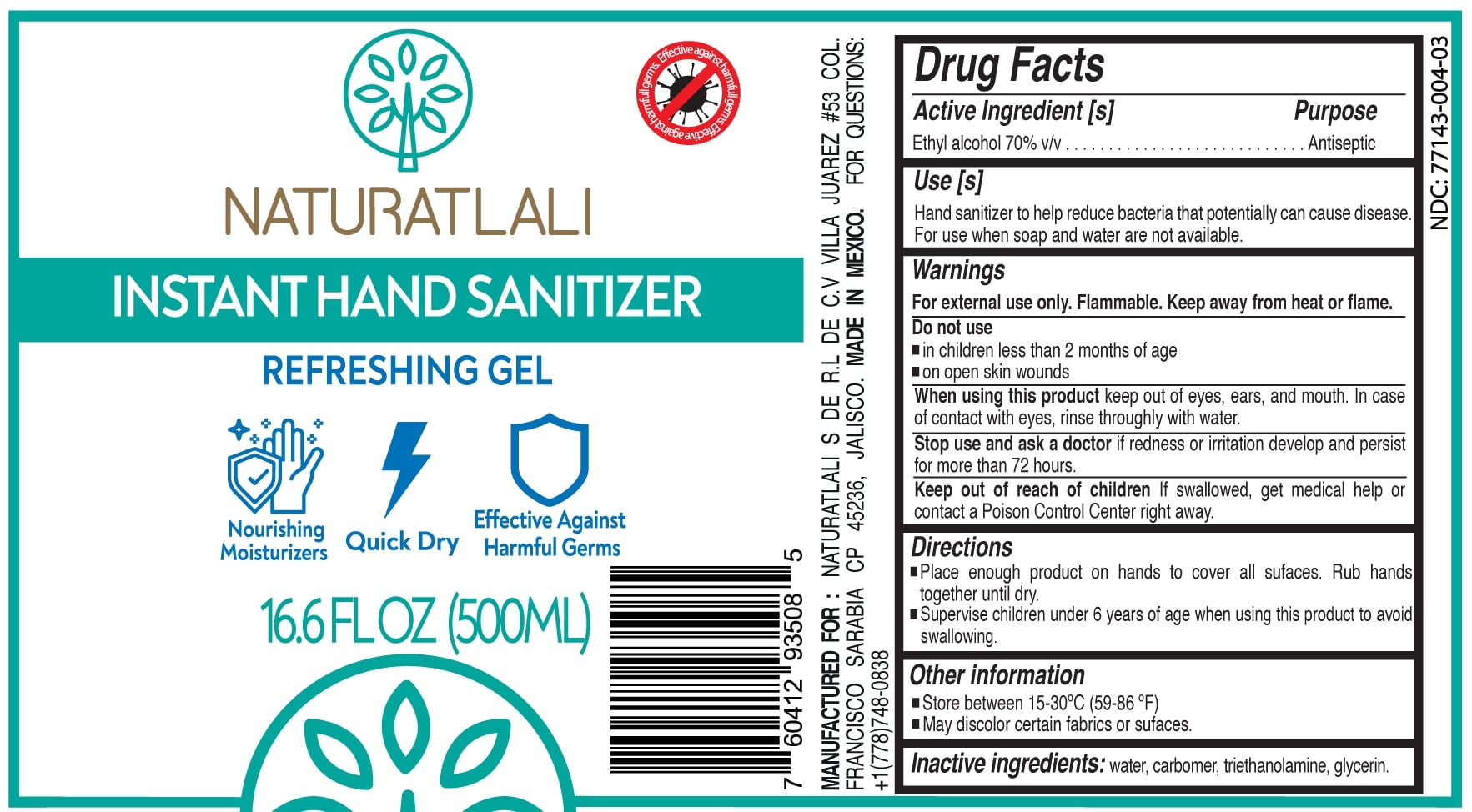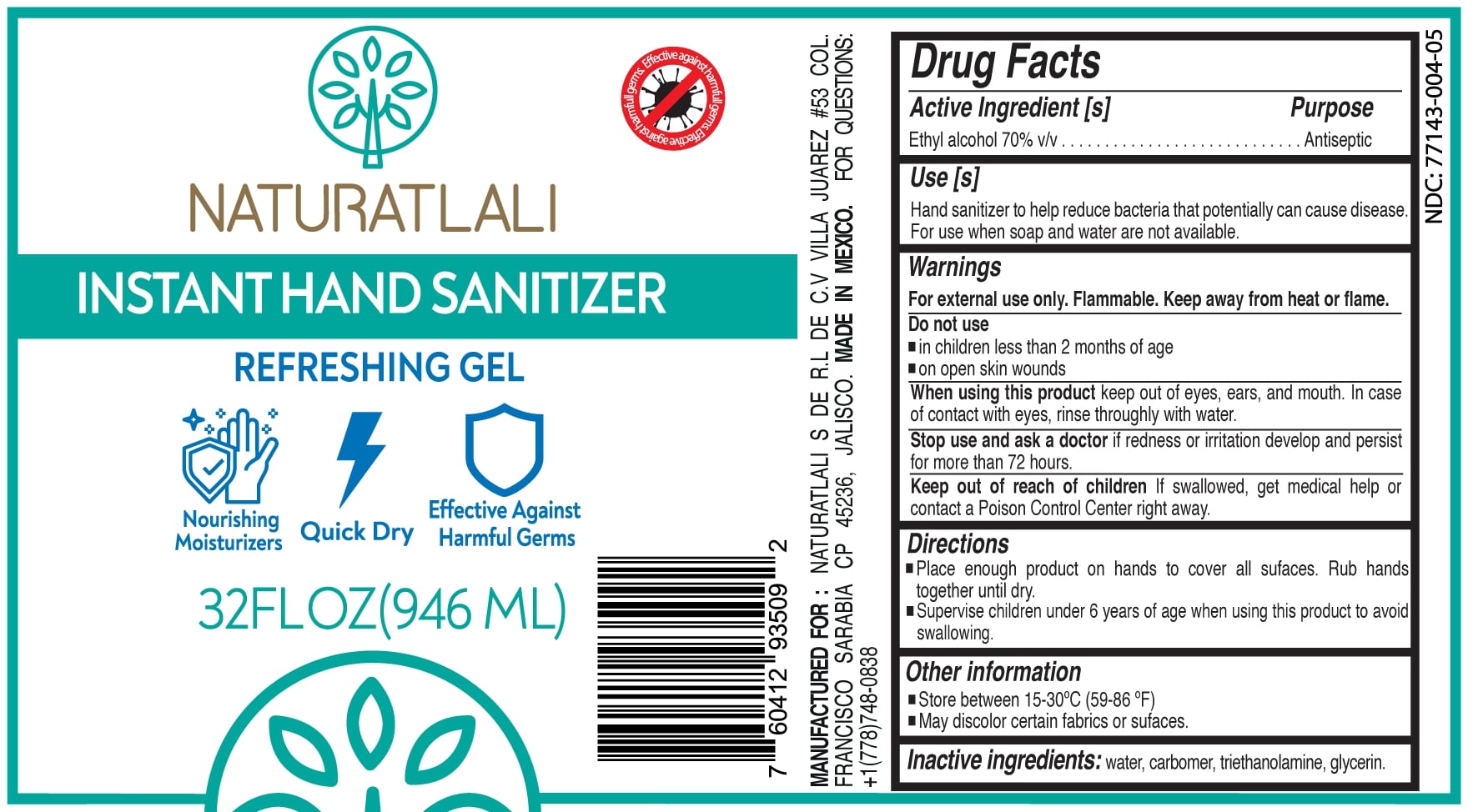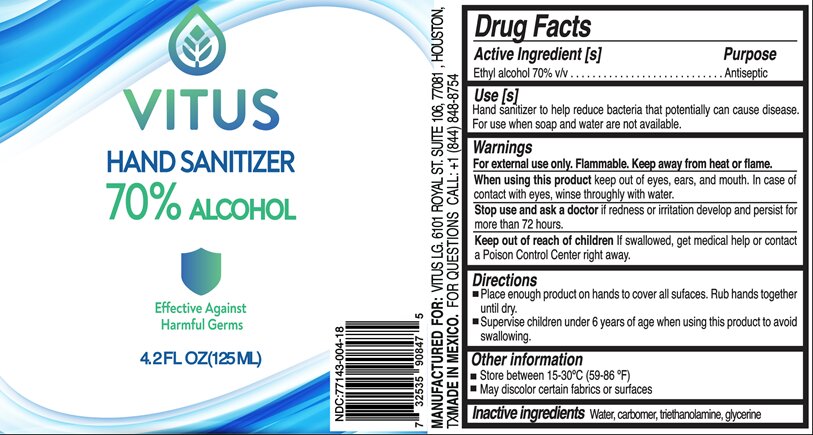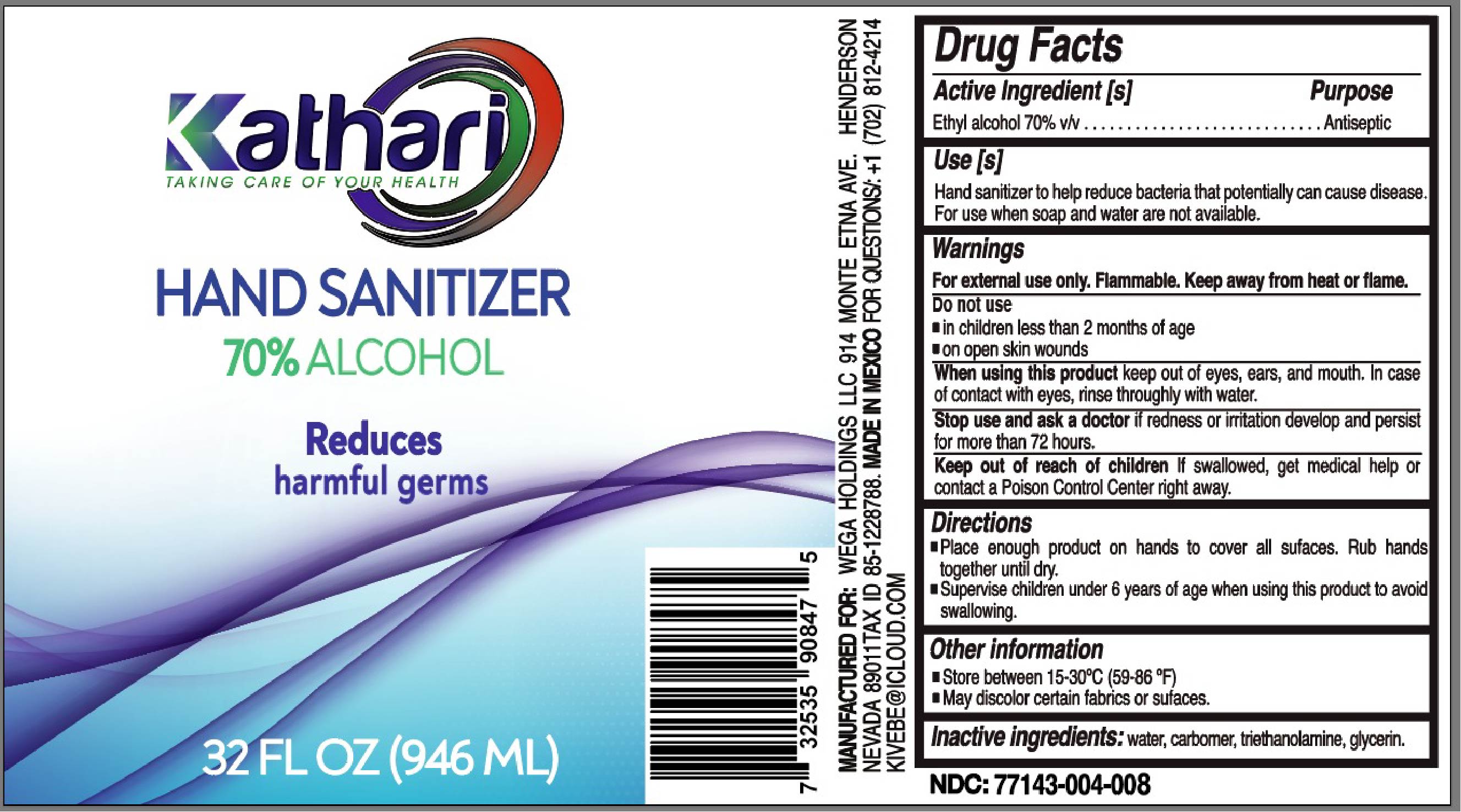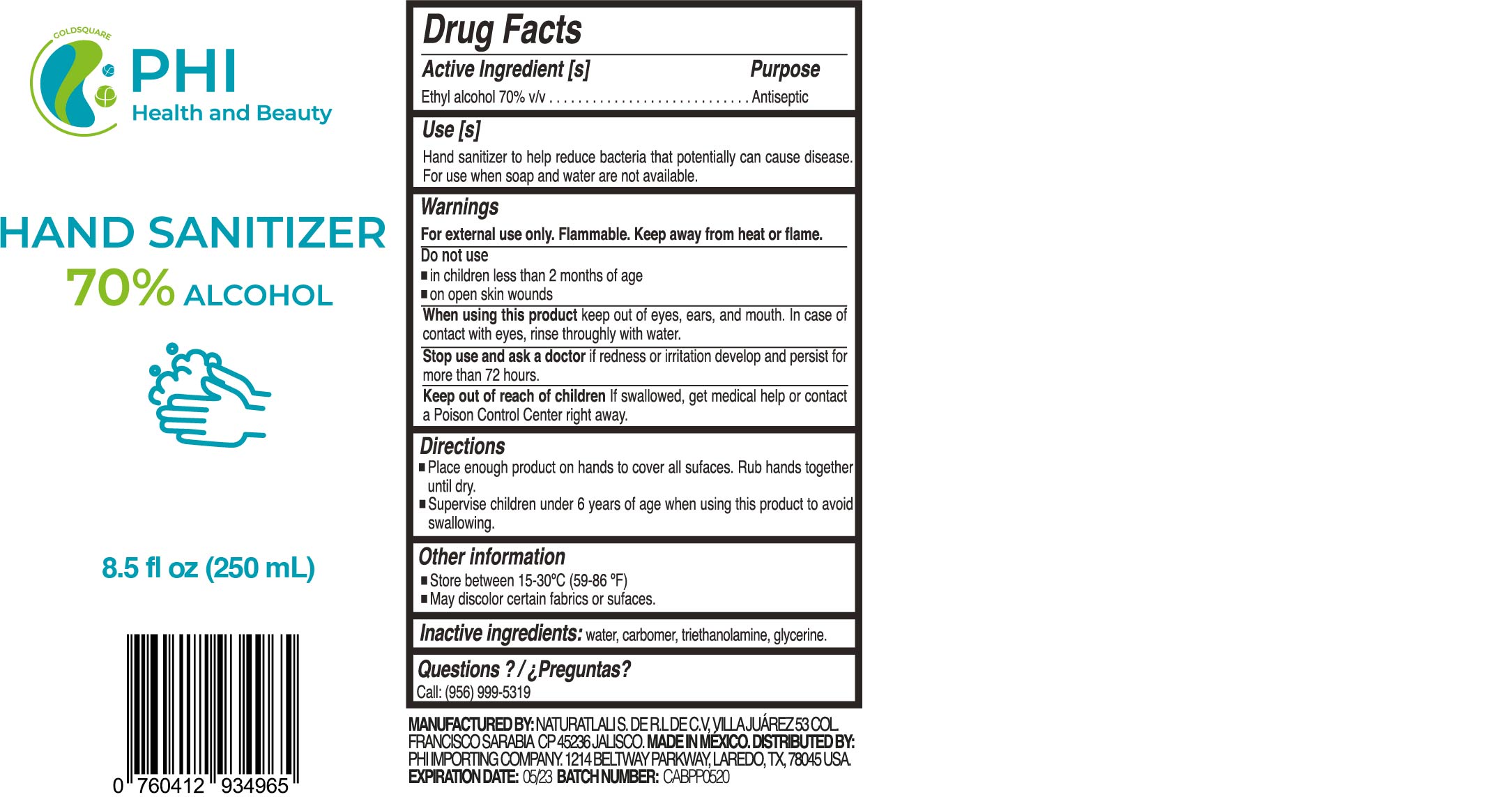 DRUG LABEL: Hand Sanitizer
NDC: 77143-004 | Form: GEL
Manufacturer: NATURATLALI S DE RL DE CV
Category: otc | Type: HUMAN OTC DRUG LABEL
Date: 20201110

ACTIVE INGREDIENTS: ALCOHOL 70 mL/100 mL
INACTIVE INGREDIENTS: GLYCERIN 2 mL/100 mL; CARBOMER 940 0.5 g/100 mL; WATER; METHYLPARABEN 0.025 g/100 mL; PROPYLPARABEN 0.025 g/100 mL; DMDM HYDANTOIN 0.025 g/100 mL; TRIETHANOLAMINE HYDRIODIDE 1 g/100 mL

77143-004 - 70% alcohol

Active Ingredient(s)

Alcohol 70% v/v. Purpose: Antiseptic

Purpose

Antiseptic, Hand Sanitizer

Use

Hand Sanitizer to help reduce bacteria that potentially can cause disease. For use when soap and water are not available.

Warnings

Flammable, keep away from fire or flame.

For external use only.

Do not use

- on open wounds

When using this product keep out of eyes, ears, and mouth. In case of contact with eyes, rinse eyes thoroughly with water.
Stop use and ask a doctor if irritation or rash occurs. These may be signs of a serious condition.
Keep out of reach of children. If swallowed, get medical help or contact a Poison Control Center right away.

Stop use and ask a doctor if irritation or rash occurs. These may be signs of a serious condition.

Keep out of reach of children. If swallowed, get medical help or contact a Poison Control Center right away.

Directions

- Place enough product on hands to cover all surfaces. Rub hands together until dry.
- Supervise children under 6 years of age when using this product to avoid swallowing.

Other information

- Store between 15-30C (59-86F)
- Avoid freezing and excessive heat above 40C (104F)

Inactive ingredients

Purified water USP, glycerin, carbomer, triethaanolamine, methylparabene, propylparabene, propylene glycol, DMDM Hydantoin.

Package Label - Principal Display Panel

946 mL NDC: 77143-004-08

250 mL NDC: 77143-004-01

236 mL NDC: 77143-004-02

3785 mL NDC: 77143-004-06

500 mL NDC: 77143-004-03

946 mL NDC: 77143-004-05

250mL NDC: 77143-004-10

3785 mL NDC: 77143-004-11

60 mL NDC: 77143-004-12

125 mL NDC: 77143-004-18